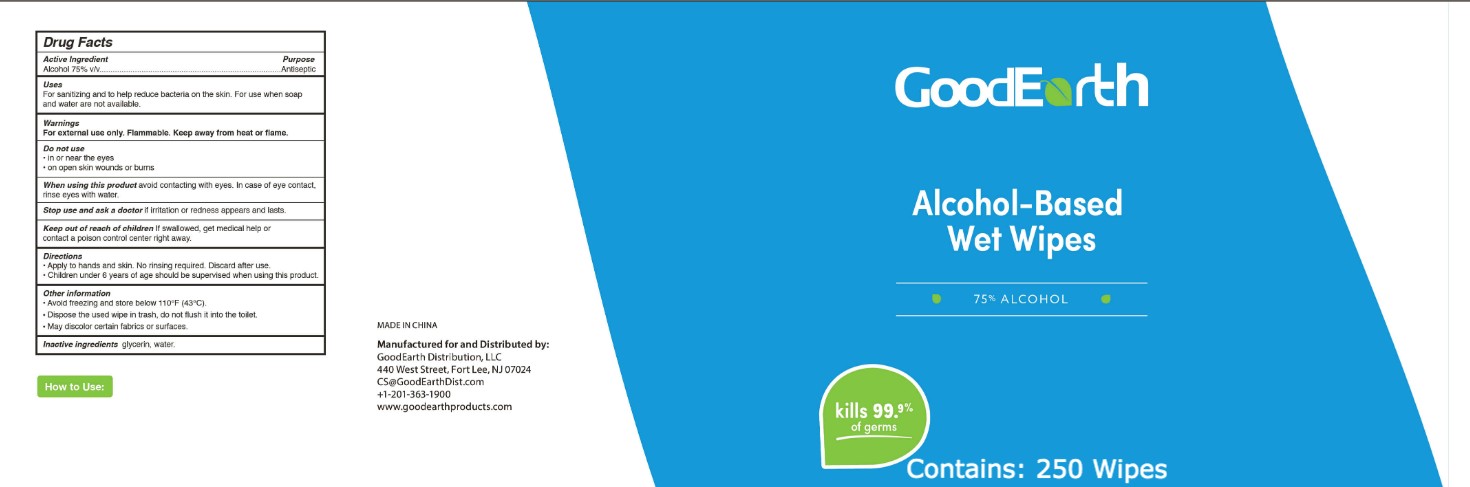 DRUG LABEL: Sanitizing Wipes
NDC: 52489-521 | Form: SWAB
Manufacturer: Imperial Palace Commodity (Shenzhen) Co., Ltd
Category: otc | Type: HUMAN OTC DRUG LABEL
Date: 20201117

ACTIVE INGREDIENTS: ALCOHOL 75 mL/100 mL
INACTIVE INGREDIENTS: GLYCERIN; WATER

Imperial Palace-GoodEarth Alcohol wipes 250-250-60-800-800-30 PCS

Active Ingredient(s)

Alcohol 75% v/v

Purpose

Antiseptic

Use

For sanitizing and to help reduce bacteria on the skin. For use when soap and water are not available.

Warnings

For external use only. Flammable. Keep away from heat or flame.

Do not use

in or near the eyes.
on open skin wounds or burns

When using this product keep out of eyes, ears, and mouth. In case of contact with eyes, rinse eyes thoroughly with water.
Stop use and ask a doctor if irritation or rash occurs. These may be signs of a serious condition.
Keep out of reach of children. If swallowed, get medical help or contact a Poison Control Center right away.

Stop use and ask a doctor if irritation or rash occurs. These may be signs of a serious condition.

Keep out of reach of children. If swallowed, get medical help or contact a Poison Control Center right away.

Directions

- Apply to hands and skin. No rinsing required. Discard after use.
- Children under 6 years of age should be supervised when using this product.

Other information

- Avoid freezing and store below 110F (43C).
- Dispose the used wipe in trash, do not flush it into the toilet.
- May discolor certain fabrics or surfaces.

Inactive ingredients

glycerin, water.

Package Label - Principal Display Panel

250 PCS NDC: 52489-521-01